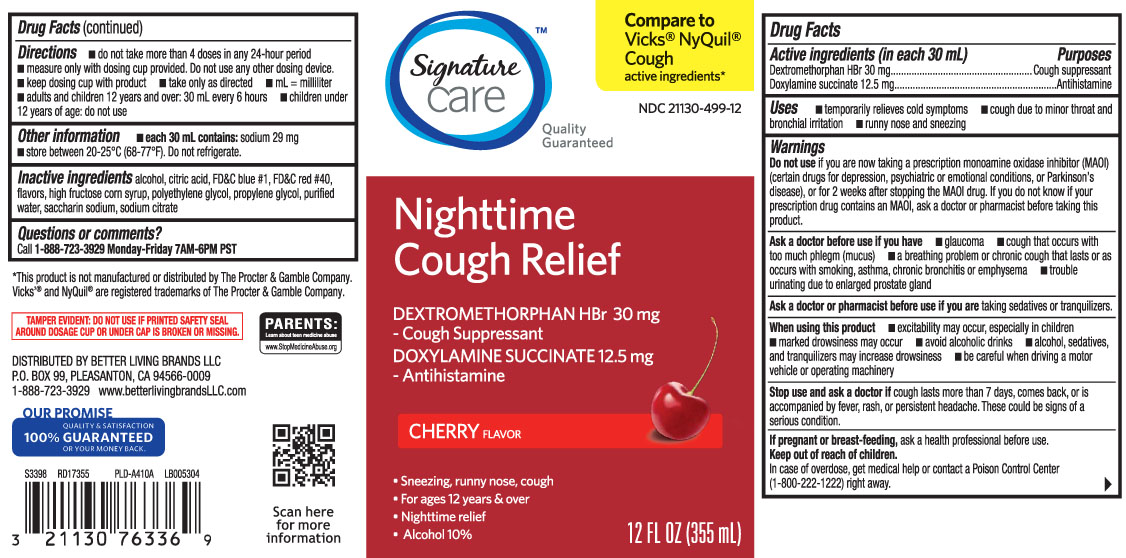 DRUG LABEL: Night Time Cough
NDC: 21130-499 | Form: LIQUID
Manufacturer: Safeway, Inc.
Category: otc | Type: HUMAN OTC DRUG LABEL
Date: 20240515

ACTIVE INGREDIENTS: DEXTROMETHORPHAN HYDROBROMIDE 30 mg/30 mL; DOXYLAMINE SUCCINATE 12.5 mg/30 mL
INACTIVE INGREDIENTS: ALCOHOL; ANHYDROUS CITRIC ACID; FD&C BLUE NO. 1; FD&C RED NO. 40; HIGH FRUCTOSE CORN SYRUP; POLYETHYLENE GLYCOL, UNSPECIFIED; PROPYLENE GLYCOL; WATER; SACCHARIN SODIUM; TRISODIUM CITRATE DIHYDRATE

Drug Facts

Active ingredients (in each 30 mL)

Dextromethorphan HBr 30 mg

Doxylamine succinate 12.5 mg

Purpose

Cough suppressant

Antihistamine

Uses

- temporarily relieves cold symptoms
- cough due to minor throat and bronchial irritation
- runny nose and sneezing

Warnings

Do not use

- if you are now taking a prescription monoamine oxidase inhibitor (MAOI) (certain drugs for depression, psychiatric or emotional conditions, or Parkinson’s disease), or for 2 weeks after stopping the MAOI drug. If you do not know if your prescription drug contains an MAOI, ask a doctor or pharmacist before taking this product.

Ask a doctor before use if you have

- glaucoma
- cough that occurs with too much phlegm (mucus)
- a breathing problem or chronic cough that lasts or as occurs with smoking, asthma, chronic bronchitis or emphysema
- trouble urinating due to enlarged prostate gland

Ask a doctor or pharmacist before use if you are

taking sedatives or tranquilizers.

When using this product

- excitability may occur, especially in children
- marked drowsiness may occur
- avoid alcoholic drinks
- be careful when driving a motor vehicle or operating machinery
- alcohol, sedatives, and tranquilizers may increase drowsiness

Stop use and ask a doctor if

cough lasts more than 7 days, comes back, or is accompanied by fever, rash, or persistent headache.

These could be sign of a serious condition.

If pregnant or breast-feeding,

ask a health professional before use.

Keep out of reach of children.

In case of overdose, get medical help or contact a Poison Control Center (1-800-222-1222) right away.

Directions

- do not take more than 4 doses in any 24-hours period
- measure only with dosing cup provided. Do not use any other dosing device
- keep dosing cup with product
- take only as directed
- mL = milliliter
- adults and children 12 years and over: 30 mL every 6 hours
- children under 12 years of age: do not use

Other information

- each 30 mL contains; sodium 29 mg
- store between 20-25ºC (68-77ºF). Do not refrigerate.

Inactive ingredients

alcohol, citric acid, FD&C blue 1, FD&C red 40, flavor, high fructose corn syrup, polyethylene glycol, propylene glycol, purified water, saccharin sodium, sodium citrate

Questions or comments?

Call 1-888-723-3929 Monday-Friday 7AM-6PM PST

Principal Display Panel

Compare to Vicks® NyQuil® Cough active ingredients*

NightTime Cough Relief

DEXTROMETHORPHAN HBr 30 mg - Cough Suppressant

DOXYLAMINE SUCCINATE 12.5 mg - Antihistamine

CHERRY FLAVOR

- Sneezing, runny nose, cough
- For ages 12 years & over
- Nighttime relief
- Alcohol 10%

FL OZ (mL)

*This product is not manufactured or distributed by The Proctor & Gamble Company, Vicks® and NyQuil® are registered trademarks of The Procter & Gamble Company.

TAMPER EVIDENT: DO NOT USE IF PRINTED SAFETY SEAL AROUND DOSAGE CUP OR UNDER CAP IS BROKEN OR MISSING.

DISTREBUTED BY BETTER LIVING BRANDS LLC

P.O. BOX 99, PLEASANTON, CA 94566-0009

www.betterlivingbrandsLLC.com

Product Label

SIGNATURE CARE Nighttime Cough Relief